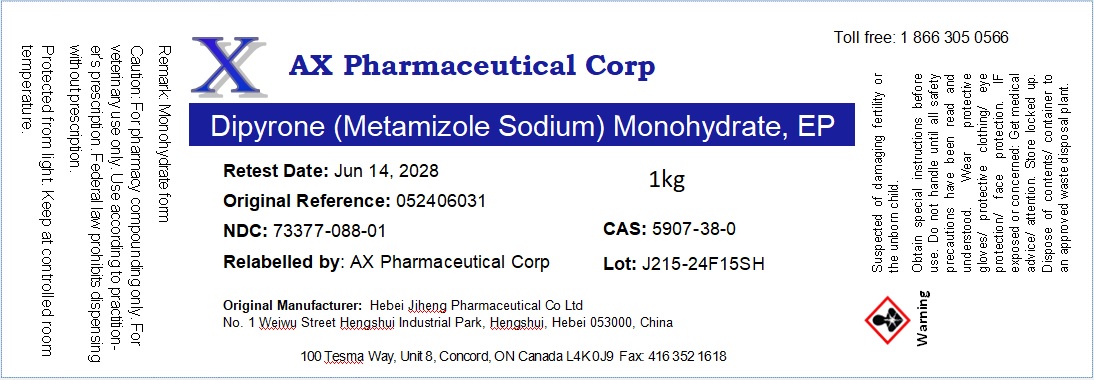 DRUG LABEL: Dipyrone (Metamizole Sodium) Monohydrate
NDC: 73377-088 | Form: POWDER
Manufacturer: AX Pharmaceutical Corp
Category: other | Type: BULK INGREDIENT - ANIMAL DRUG
Date: 20241230

ACTIVE INGREDIENTS: Metamizole Sodium 1 kg/1 kg

Dipyrone (Metamizole Sodium) Monohydrate